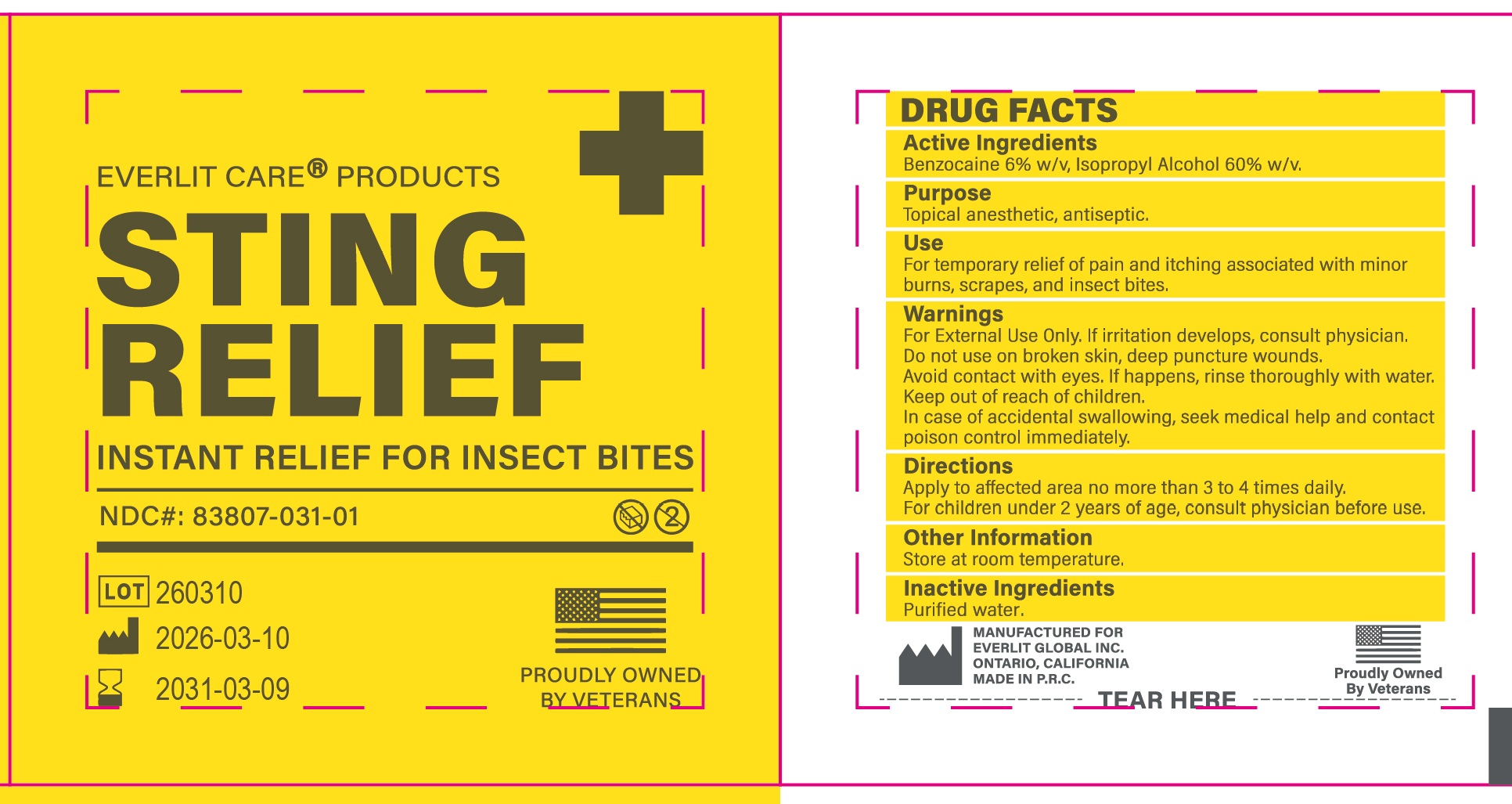 DRUG LABEL: Everlit Care Products Sting Relief
NDC: 83807-031 | Form: CLOTH
Manufacturer: EVERLIT GLOBAL INC.
Category: otc | Type: HUMAN OTC DRUG LABEL
Date: 20260209

ACTIVE INGREDIENTS: BENZOCAINE 0.024 g/1 1; ISOPROPYL ALCOHOL 0.24 g/1 1
INACTIVE INGREDIENTS: WATER

83807-031, Everlit Care Products Sting Relief Pad

ACTIVE INGREDIENT

Benocaine 6% w/v, lsopropyl Alcohol 60% w/v

PURPOSE

Topical anesthetic, antiseptic

USES

For temporary relief of pain and itching associated with minor burns, scrapes, and insect bites

WARNINGS

For external use only. If irritation develops, consult a physician

Do not use on broken skin, deep puncture wounds

Avoid contact with eyes. If happens, rinse thoroughly with water

Keep out of reach of children. In case of accidental swallowing, seek medical help and contacta Poison Control Center immediately.

Directions

Apply to affected area no more than 3 or 4 times daily.

For children under 2 years of age, consult physician before use.

Other Information

Store at room temperature

INACTIVE INGREDIENT

Purified water